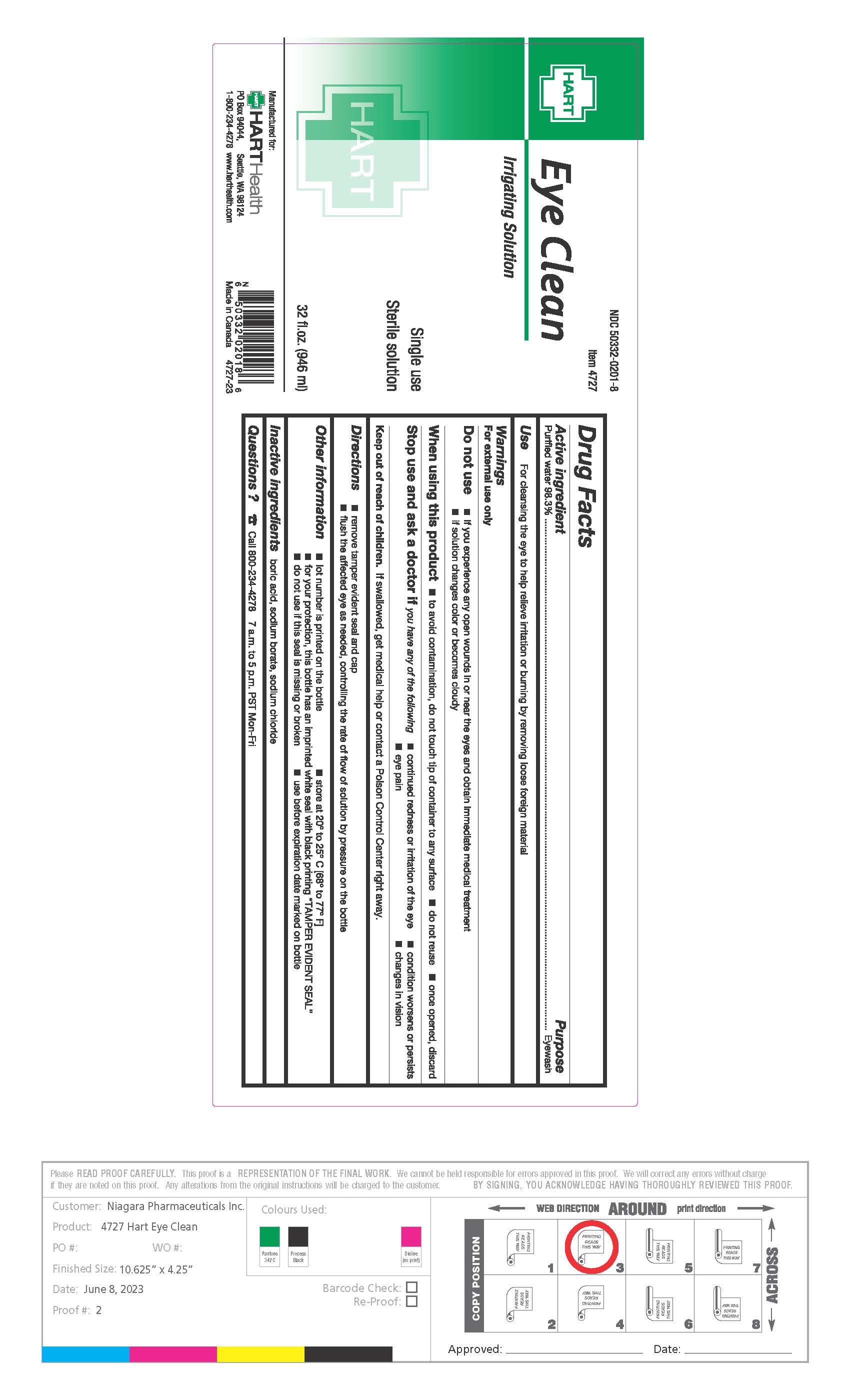 DRUG LABEL: Eye Clean
NDC: 50332-0201 | Form: LIQUID
Manufacturer: HART Health
Category: otc | Type: HUMAN OTC DRUG LABEL
Date: 20251231

ACTIVE INGREDIENTS: WATER 98.3 mL/100 mL
INACTIVE INGREDIENTS: BORIC ACID; SODIUM BORATE; SODIUM CHLORIDE

Active Ingredient: Purified Water 98.3%

Purpose: Eyewash

INDICATIONS AND USAGE

Use: For cleansing the eye to help relieve irritation or burning by removing loose foreign material

Warnings: For external use only

Do not use:

- if you experience any open wounds in or near the eyes and obtain immediate medical treatment
- if solution changes color or becomes cloudy

When using this product:

- to avoid contamination, do not touch tip of container to any surface
- do not reuse
- once opened, discard

Stop use and ask a doctor if you experience:

- changes in vision
- eye pain
- condition worsens or persists
- continued redness or irration of the eye

Keep out of reach of children. If swallowed, get medical help or contact a Poison Control Center right away.

DOSAGE AND ADMINISTRATION

Directions: Flush the affeced eye as needed, controlling the rate of flow of solution by pressure on the bottle.

Inactive Ingredients: Boric Acid, Sodium Borate, Sodium Chloride